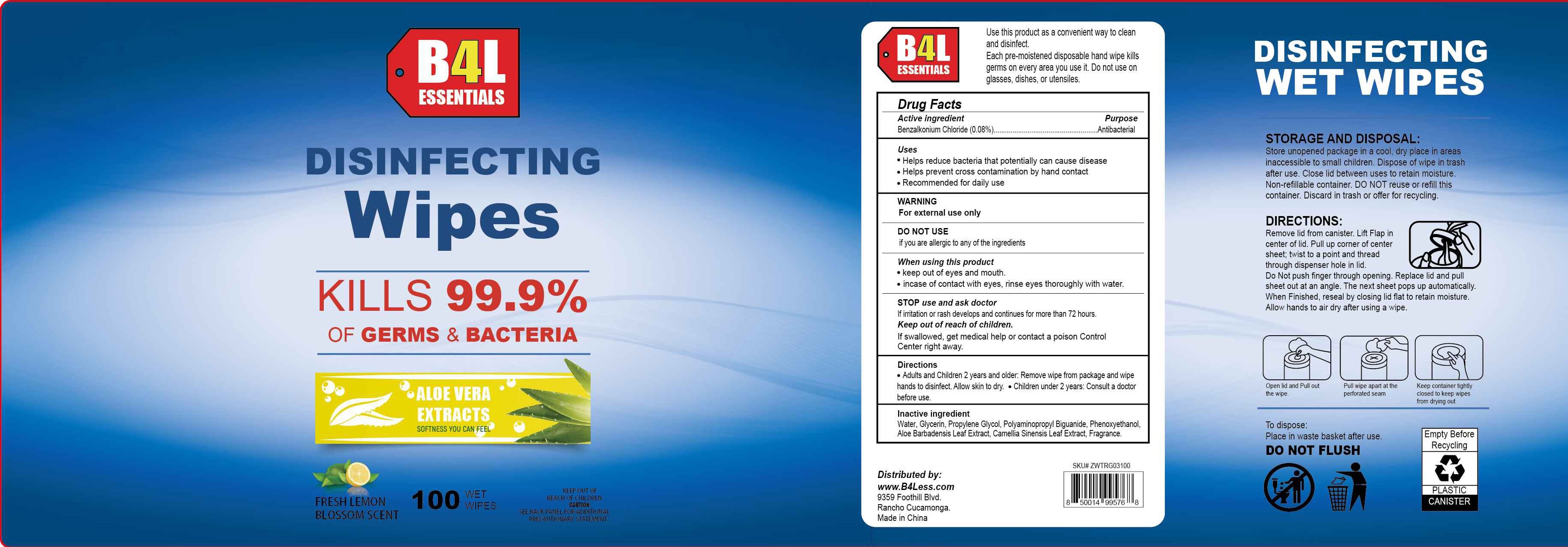 DRUG LABEL: Disinfecting Wipes
NDC: 77435-112 | Form: SWAB
Manufacturer: HAINING LILY CLEANING PRODUCTS CO., LTD
Category: otc | Type: HUMAN OTC DRUG LABEL
Date: 20200728

ACTIVE INGREDIENTS: BENZALKONIUM CHLORIDE 0.08 g/100 g
INACTIVE INGREDIENTS: water; PROPYLENE GLYCOL; GLYCERIN; AMINOMETHYLPROPANOL; ALOE VERA LEAF; POLYAMINOPROPYL BIGUANIDE; PHENOXYETHANOL

Antibacterial Wipes

Active Ingredient

BENZALKONIUM CHLORIDE 0.08

Purpose

Antibacterial

INDICATIONS AND USAGE

- helps reduce bacteria that potentially can cause disease
- Helps prevent cross contamination by hand contact
- Recommended for daily use

Warning

- For external use only.
- Flammable, keep away from heat and flame
- Do not sue if you are allergic to any of the ingredients.
- When uising this product keep out of eyes, and mouth. In case of contact with eyes, rinse eyes thoroughly with water.
- Stop use and ask a doctor if irritation or rash develops and continues for more than 72 hours.

KEEP OUT OF REACH OF CHILDREN

If swallowed,, get medical help or contact a poison control center right away.

direction

- Adults and children 2 years and older: Remove wipe fro package and wipe hands to disinfect. Allow skin to dry.
- Children under 2 years: consult a doctor before use.

Inactive ingredients

Water, Glycerin, Propylene Glycol, Polyaminopropyl Biguanide, Phenoxyethanol, Benzalkonium Chloride, Aloe Barbadensis Leaf Extract, Camellia Sinensis Leaf Extract, Fragrance